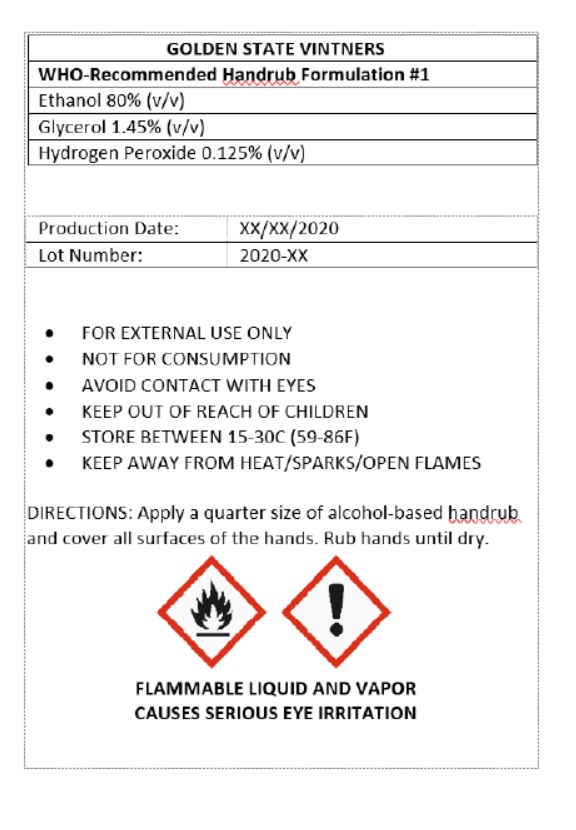 DRUG LABEL: TWG WHO Handrub
NDC: 78029-101 | Form: LIQUID
Manufacturer: Golden State Vintners
Category: otc | Type: HUMAN OTC DRUG LABEL
Date: 20200521

ACTIVE INGREDIENTS: ALCOHOL 80 L/100 L
INACTIVE INGREDIENTS: GLYCERIN; HYDROGEN PEROXIDE

TWG WHO Handrub

ACTIVE INGREDIENT

Ethanol 80% (v/v)

PURPOSE

Antiseptic

INACTIVE INGREDIENT

Glycerol 1.45% (v/v)

Hydrogen Peroxide 0.125% (v/v)

INDICATIONS AND USAGE

Hand Sanitizer

WARNINGS

- FOR EXTERNAL USE ONLY
- NOT FOR CONSUMPTION
- AVOID CONTACT WITH EYES
- KEEP AWAY FROM HEAT/SPARKS/OPEN FLAMES

- KEEP OUT OF REACH OF CHILDREN

STORAGE AND HANDLING

- STORE BETWEEN 15-30C (59-86F)

DOSAGE AND ADMINISTRATION

DIRECTIONS: Apply a quarter size of alcohol-based handrub and cover all surfaces of the hands. Rub hands until dry.

GOLDEN STATE VINTNERS

WHO-Recommended Handrub Formulation #1

FLAMMABLE LIQUID AND VAPOR CAUSES SERIOUS EYE IRRITATION